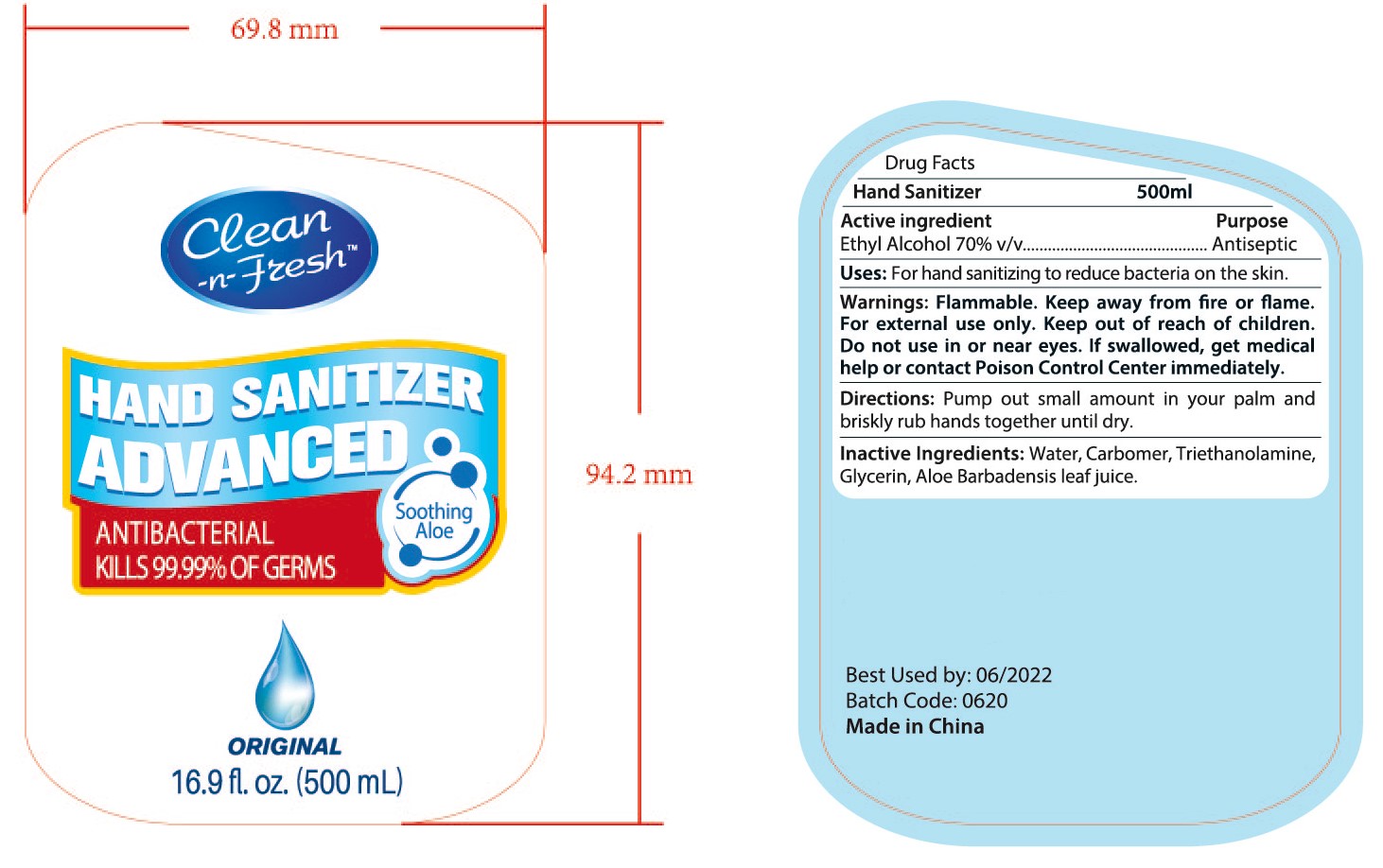 DRUG LABEL: HAND SANITIZER
NDC: 47993-283 | Form: GEL
Manufacturer: NINGBO JIANGBEI OCEAN STAR TRADING CO.,LTD
Category: otc | Type: HUMAN OTC DRUG LABEL
Date: 20201105

ACTIVE INGREDIENTS: ALCOHOL 70 mL/100 mL
INACTIVE INGREDIENTS: WATER; CARBOMER 940; TRIETHANOLAMINE BENZOATE; ALOE VERA LEAF; GLYCERIN

47993-283

Active ingredients

Ethyl Alcohol 70% v/v

PURPOSE

Antiseptic

Uses：

For hand sanitizing to reduce bacteria on the skin.

Warnings:

Flammable. Keep away from fire or flame. For external use only. Keep out of reach of children.Do not use in or near eyes. If swallowed, get medical help or contact Poison Control Center immediately.

Keep out of reach of children.

Directions:

Pump out small amount in your palm and briskly rub hands together until dry.

Inactive Ingredients:

Water,Carbomer,Triethanolamine,Glycerin,Aloe Barbadensis leaf juice.